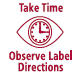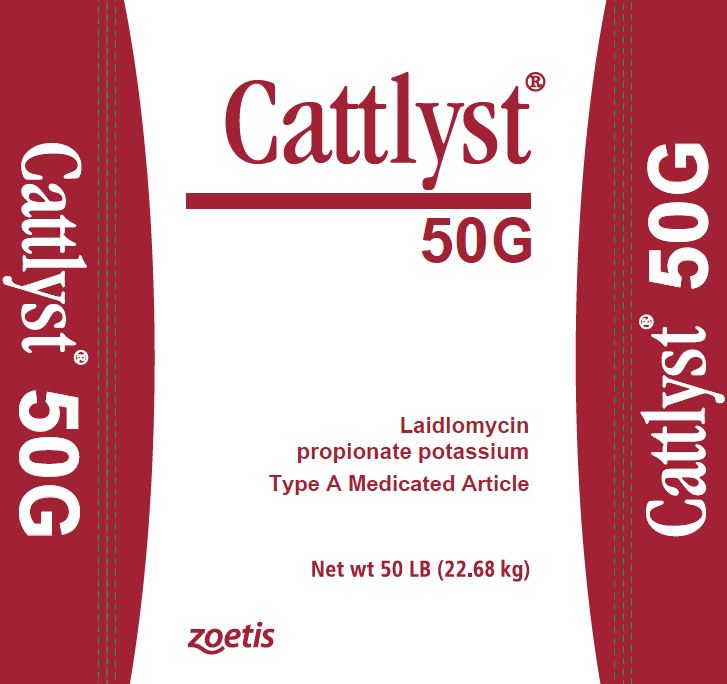 DRUG LABEL: Cattlyst
NDC: 54771-2000 | Form: GRANULE
Manufacturer: Zoetis Inc.
Category: animal | Type: OTC TYPE A MEDICATED ARTICLE ANIMAL DRUG LABEL
Date: 20220902

ACTIVE INGREDIENTS: LAIDLOMYCIN PROPIONATE POTASSIUM 50 g/0.45 kg

Cattlyst®
50G

Laidlomycin propionate potassium

Type A Medicated Article

Net wt 50 LB (22.68 kg)

For improved feed efficiency and increased rate of weight gain in cattle fed in confinement for slaughter.

Active Drug Ingredient

Laidlomycin propionate potassium, 50 grams per pound, in a carrier suitable for incorporation in feed.

.

Weight Gain and Feed Efficiency

For increased rate of weight gain and improved feed efficiency when incorporated into complete cattle feed at 5 g/ton to provide not less than 30 mg and not more than 75 mg per head per day.

Feed Efficiency

For improved feed efficiency when incorporated into complete cattle feed at 5 to 10 g/ton to provide not less than 30 mg and not more than 150 mg per head per day.

Mixing And Feeding Instructions

Read all directions carefully before mixing and feeding.

DO NOT FEED UNDILUTED

Type B Medicated Feed

Thoroughly mix the following amounts of Cattlyst 50G to make one ton of Type B Medicated Feed to provide the concentrations shown in TABLE 1. With low use levels of Cattlyst 50G (e.g. two lb/ton or less), the use of an intermediate blending step should be performed to ensure adequate mixing.

Liquid feeds made with Cattlyst 50G shall have a dry matter content in the range of 62%-75%, pH in the range of 6.0-8.0 and drug level of 100-2000 g/ton. Its label shall carry daily and prior to use recirculating/agitation directions and an expiration of 21 days from date of manufacture. The Type C feed made with this Type B liquid feed shall be fed within seven days from date of manufacture.

TABLE 1 - Type B Medicated Feed
Pounds of Cattlyst 50G per ton of supplement | Laidlomycin Concentration in Type B Medicated Feed (Grams per ton)
2.0 | 100
4.0 | 200
20.0 | 1000
40.0 | 2000

Type C Medicated Feed

Thoroughly mix the following amounts of Cattlyst 50G to make one ton of Type C Medicated Feed that provides 5-10 grams of laidlomycin propionate potassium per ton of feed on a 90% dry matter basis (TABLE 2). An intermediate blending step should be performed to ensure adequate mixing. For example, use one part Cattlyst 50G Type A Medicated Article with nine parts of feed ingredients to prepare an intermediate blend before preparing a Type C Medicated Feed. Feed continuously in the range of 5-10 grams per ton to growing and finishing beef cattle.

TABLE 2 - Type C Medicated Feed
Pounds of Cattlyst 50G per ton of complete feed | Pounds of a 1,000 g/ton Type B Medicated Feed per ton of complete feed | Laidlomycin Concentration in complete Type C feed 90% dry matter basis (grams per ton)
0.1 | 10 | 5
0.15 | 15 | 7.5
0.20 | 20 | 10

Caution

Do not allow horses or other equines access to feeds containing laidlomycin propionate potassium (Cattlyst 50G). The safety of laidlomycin propionate potassium (Cattlyst 50G) in unapproved species has not been established.

Not for use in animals intended for breeding.

WARNING

When mixing and handling Cattlyst 50G use appropriate protective clothing, eye, face, and respiratory protection. If accidental eye or skin contact occurs, rinse immediately with water. Operators should wash thoroughly with soap and water after handling Cattlyst 50G.

Keep container closed between uses.

Store below 25°C (77°F), excursions permitted to 37°C (99°F).

Restricted Drug (California) - Use Only as Directed. Not for human use.

Approved by FDA under NADA # 141-025

zoetis
Distributed by:
Zoetis Inc.
Kalamazoo, MI 49007

Net wt 50 LB (22.68 kg)